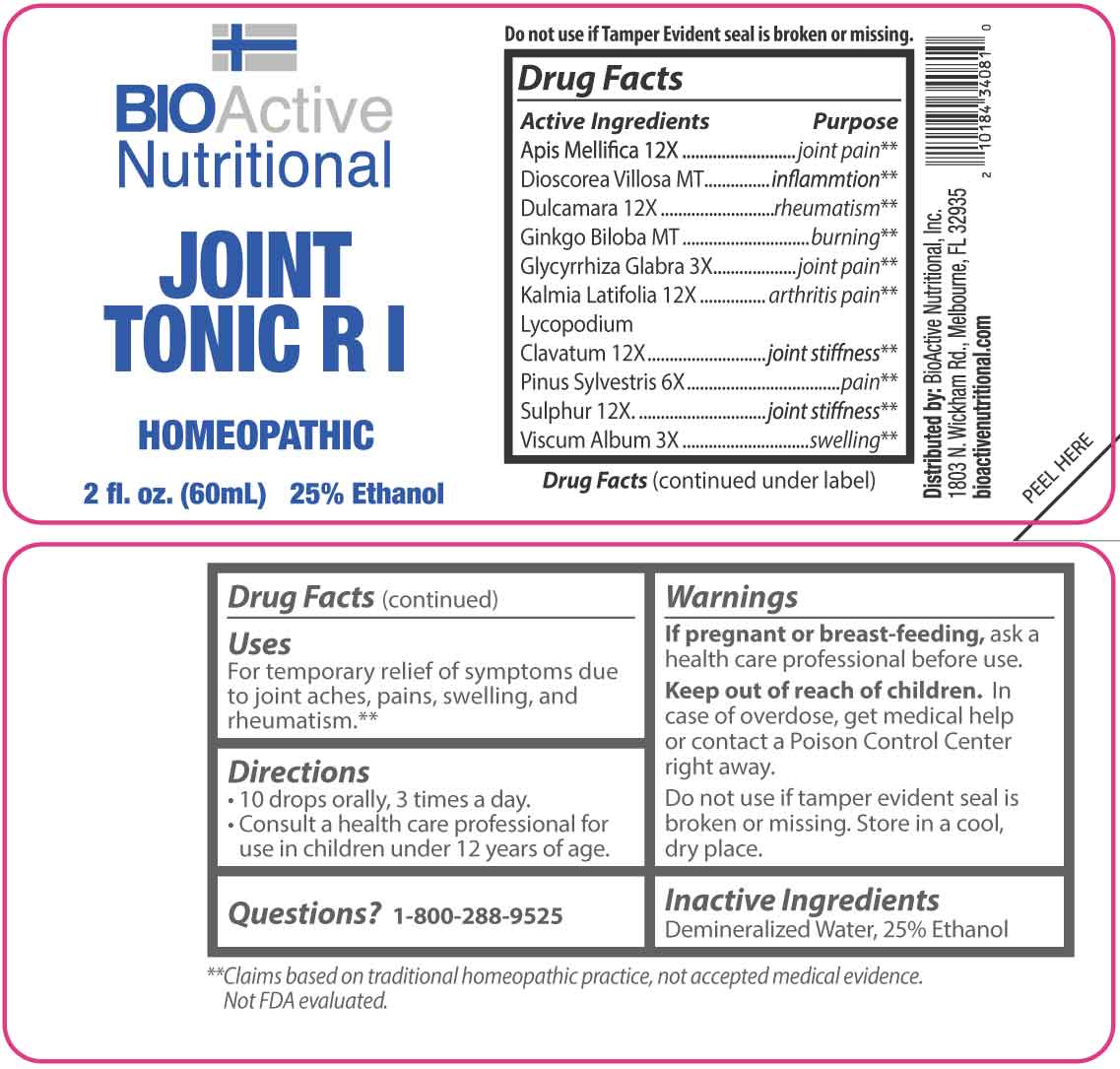 DRUG LABEL: Joint Tonic R I
NDC: 43857-0664 | Form: LIQUID
Manufacturer: BioActive Nutritional, Inc.
Category: homeopathic | Type: HUMAN OTC DRUG LABEL
Date: 20260121

ACTIVE INGREDIENTS: GINKGO 1 [hp_X]/1 mL; DIOSCOREA VILLOSA TUBER 1 [hp_X]/1 mL; GLYCYRRHIZA GLABRA (LICORICE) ROOT POWDER 3 [hp_X]/1 mL; VISCUM ALBUM FRUITING TOP 3 [hp_X]/1 mL; PINUS SYLVESTRIS LEAFY TWIG 6 [hp_X]/1 mL; APIS MELLIFERA 12 [hp_X]/1 mL; SOLANUM DULCAMARA TOP 12 [hp_X]/1 mL; KALMIA LATIFOLIA LEAF 12 [hp_X]/1 mL; LYCOPODIUM CLAVATUM SPORE 12 [hp_X]/1 mL; SULFUR 12 [hp_X]/1 mL
INACTIVE INGREDIENTS: WATER; ALCOHOL

DRUG FACTS:

ACTIVE INGREDIENTS:

Apis Mellifica 12X, Dioscorea Villosa MT, Dulcamara 12X, Ginkgo Biloba MT, Glycyrrhiza Glabra 3X, Kalmia Latifolia 12X, Lycopodium Clavatum 12X, Pinus Sylvestris 6X, Sulphur 12X, Viscum Album 3X.

PURPOSE:

Apis Mellifica – joint pain,** Dioscorea Villosa - inflammation,** Dulcamara - rheumatism,** Ginkgo Biloba - burning,** Glycyrrhiza Glabra – joint pain,** Kalmia Latifolia – arthritis pain,** Lycopodium Clavatum – joint stiffness,** Pinus Sylvestris - pain,** Sulphur – joint stiffness,** Viscum Album – swelling**

**Claims based on traditional homeopathic practice, not accepted medical evidence. Not FDA evaluated.

USES:

For temporary relief of symptoms due to joint aches, pains, swelling, and rheumatism.**

**Claims based on traditional homeopathic practice, not accepted medical evidence. Not FDA evaluated.

WARNINGS:

If pregnant or breast-feeding, ask a health care professional before use.

Keep out of reach of children. In case of overdose, get medical help or contact a Poison Control Center right away.

Do not use if tamper evident seal is broken or missing.

Store in a cool, dry place.

KEEP OUT OF REACH OF CHILDREN:

In case of overdose, get medical help or contact a Poison Control Center right away.

DIRECTIONS:

• 10 drops orally, 3 times a day.

• Consult a health care professional for use in children under 12 years of age.

INACTIVE INGREDIENTS:

Demineralized Water, 25% Ethanol

QUESTIONS:

Distributed by:

BioActive Nutritional, Inc.

1803 N. Wickham Rd.

Melbourne, FL 32935

bioactivenutritional.com

1-800-288-9525

PACKAGE LABEL DISPLAY:

BIOActive Nutritional

JOINT TONIC R I

HOMEOPATHIC

2 fl. oz. (60mL)